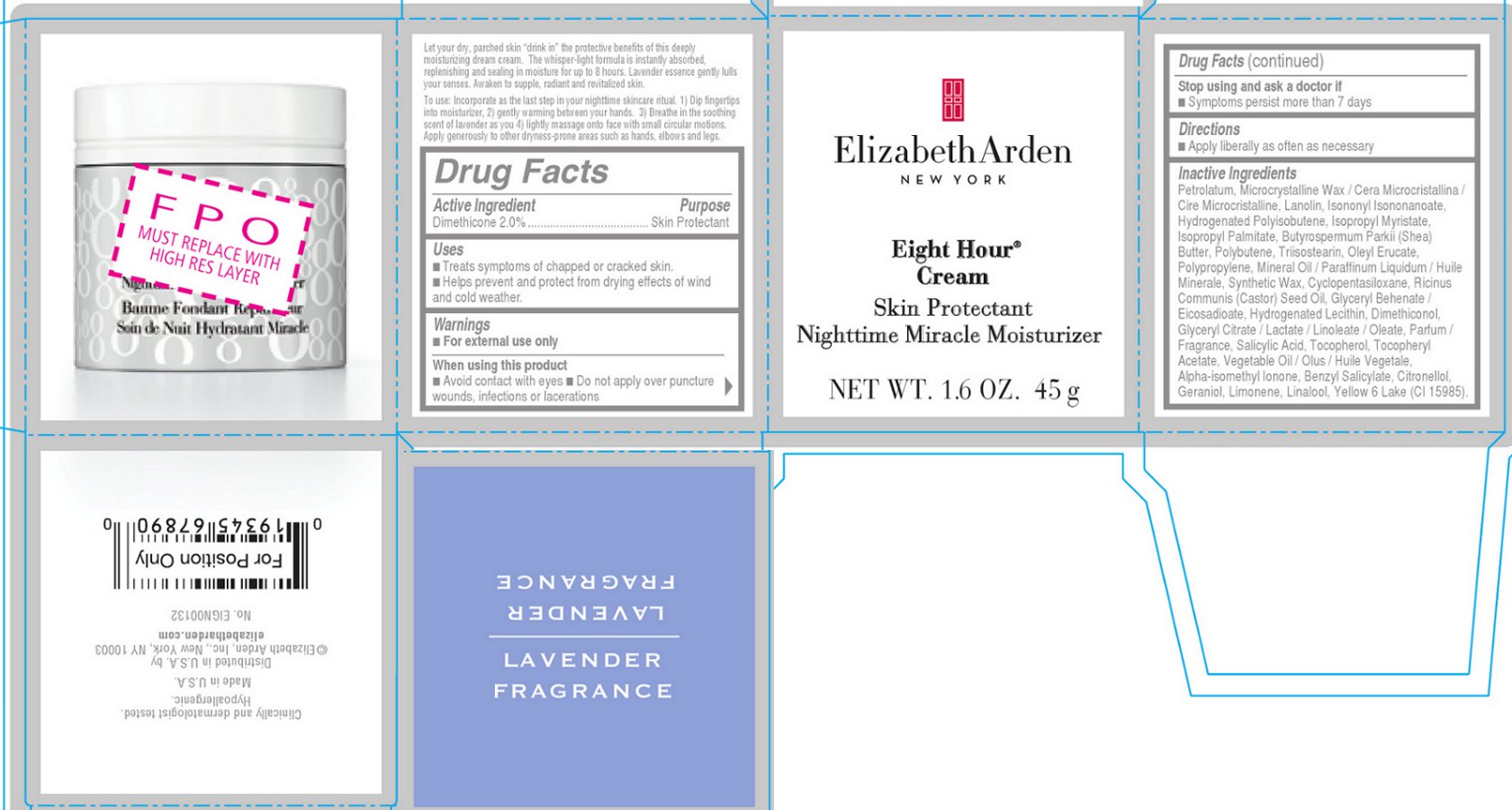 DRUG LABEL: EIGHT HOUR CREAM SKIN PROTECTANT NIGHTTIME MIRACLE MOISTURIZER
NDC: 67938-2001 | Form: CREAM
Manufacturer: Elizabeth Arden, Inc
Category: otc | Type: HUMAN OTC DRUG LABEL
Date: 20130729

ACTIVE INGREDIENTS: DIMETHICONE 0.9 g/45 g
INACTIVE INGREDIENTS: PETROLATUM; MICROCRYSTALLINE WAX; LANOLIN; ISONONYL ISONONANOATE; ISOPROPYL MYRISTATE; ISOPROPYL PALMITATE; POLYBUTENE (1400 MW); TRIISOSTEARIN; OLEYL ERUCATE; MINERAL OIL; SYNTHETIC WAX (1200 MW); GLYCERYL BEHENATE/EICOSADIOATE; DIMETHICONOL (40 CST); GLYCERYL CITRATE; SALICYLIC ACID; TOCOPHEROL; BENZYL SALICYLATE; CITRONELLOL ACETATE, (R)-; GERANIOL

242214

DESCRIPTION

The whisper-light formula is instantly absorbed, replenishing and sealing in moisture for up to 8 hours. Lavender essence gently lulls your senses. Awaken to supple, radiant and revitalized skin.

INDICATIONS AND USAGE

To use: Incorporate as the last step in your nighttime skincare ritual. 1) Dip fingertips into moisturizer, 2) gently warming between your hands. 3) Breathe in the soothing scent of lavender as you 4) lightly massage onto face with small circular motions. Apply generously to other dryness-prone areas such as hands, elbows and legs.

WARNINGS

For external use only

OTC - ACTIVE INGREDIENT

Dimethicone 2.0%...................................... Skin Protectant

INACTIVE INGREDIENT

Inactive Ingredients

Petrolatum, Microcrystalline Wax / Cera Microcristallina /Cire Microcristalline, Lanolin, Isononyl Isononanoate, Hydrogenated Polyisobutene, Isopropyl Myristate, Isopropyl Palmitate, Butyrospermum Parkii (Shea) Butter, Polybutene, Triisostearin, Oleyl Erucate, Polypropylene, Mineral Oil / Paraffinum Liquidum / Huile Minerale, Synthetic Wax, Cyclopentasiloxane, Ricinus Communis (Castor) Seed Oil, Glyceryl Behenate / Eicosadioate, Hydrogenated Lecithin, Dimethiconol, Glyceryl Citrate / Lactate / Linoleate / Oleate, Parfum /Fragrance, Salicylic Acid, Tocopherol, Tocopheryl Acetate, Vegetable Oil / Olus / Huile Vegetale, Alpha-isomethyl Ionone, Benzyl Salicylate, Citronellol, Geraniol, Limonene, Linalool, Yellow 6 Lake (CI 15985).

DOSAGE AND ADMINISTRATION

Massage onto face.

OTC - KEEP OUT OF REACH OF CHILDREN

Keep out of reach of children

OTC - PURPOSE

Skin Protection

OTC - WHEN USING

Avoid contact with eyes Do not apply over puncture wounds, infections or lacerations